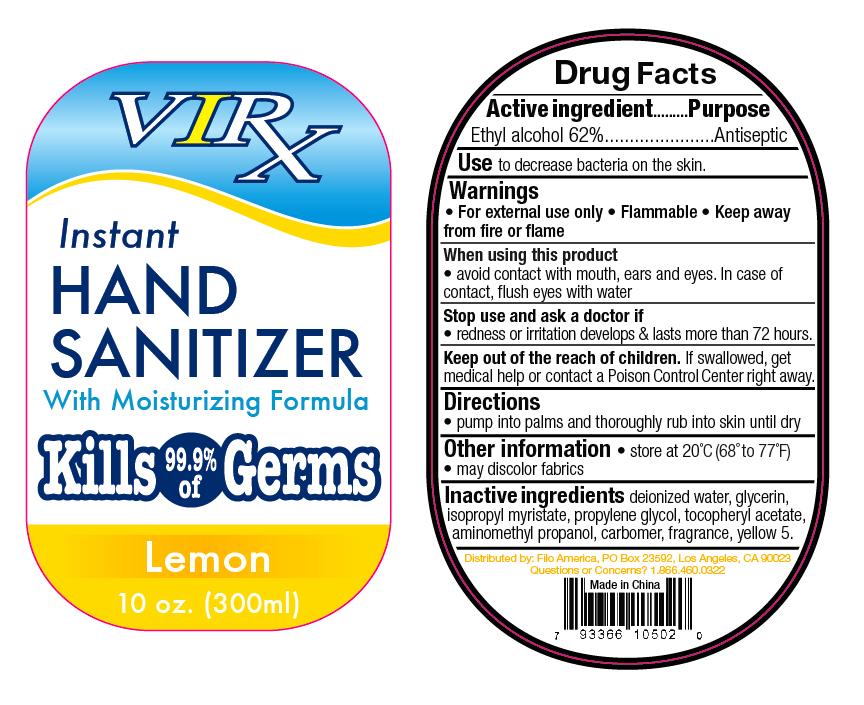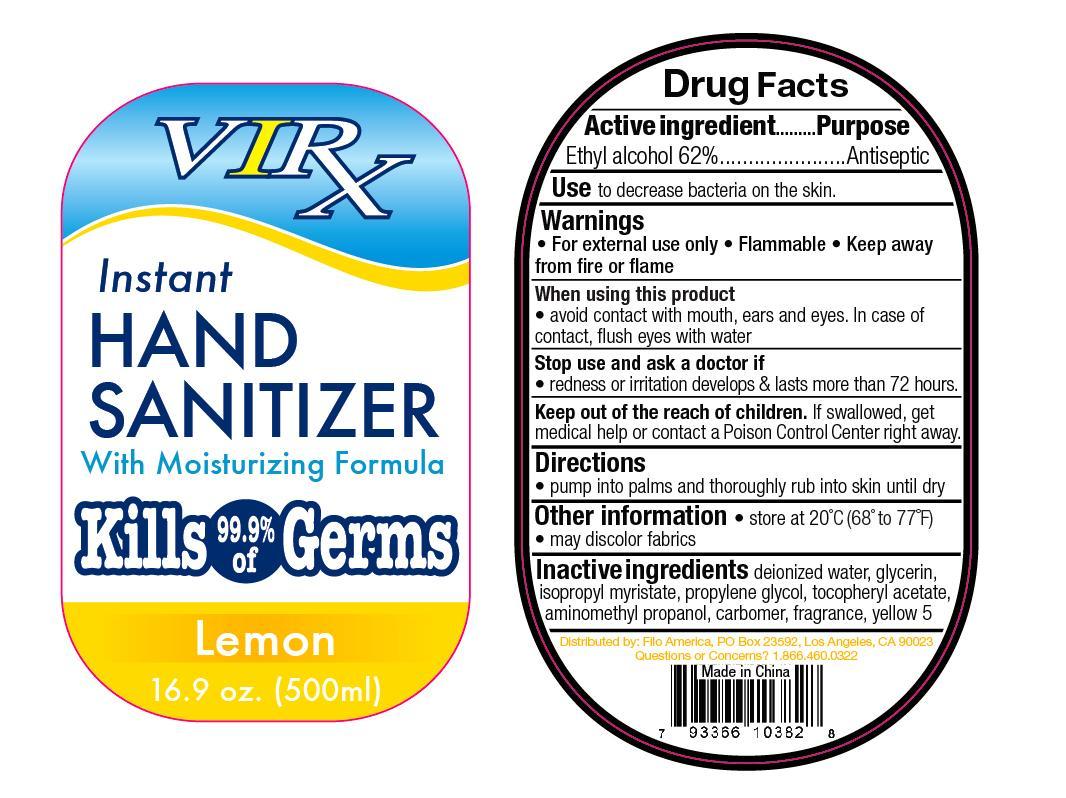 DRUG LABEL: Virx
NDC: 50438-807 | Form: GEL
Manufacturer: Filo America
Category: otc | Type: HUMAN OTC DRUG LABEL
Date: 20100323

ACTIVE INGREDIENTS: Alcohol 496 mL/800 mL
INACTIVE INGREDIENTS: Carbomer 934

Virx Instant Hand Sanitizer Drug Facts

Active Ingredient...........................................................Purpose
Ethyl Alcohol 62%...........................................................................Antiseptic

PURPOSE

Use to decrease bacteria on the skin.

Warnings
For external use only * Flammable * Keep away from fire or flame.

When using this product avoid contact with mouth, ears, and eyes. In case of contact, flush eyes with water.

Stop use and ask a doctor if redness or irritation develops and lasts more than 72 hours.

KEEP OUT OF REACH OF CHILDREN

Keep out of the reach of children. If swallowed, get medical help or contact a Poison Control Center right away.

Directions
Pump into palms and thoroughly rub into skin until dry.

Other Information * store at 20 degrees Celcius (68 degrees to 77 degrees Farenheit) * may discolor fabrics.

INACTIVE INGREDIENT

Deionized water, glycerin, isopropyl myristate, propylene glycol, tocopheryl acetate, aminomethyl propanol, carbomer, fragrance and yellow 5.

PACKAGE LABEL

MM1
MM2